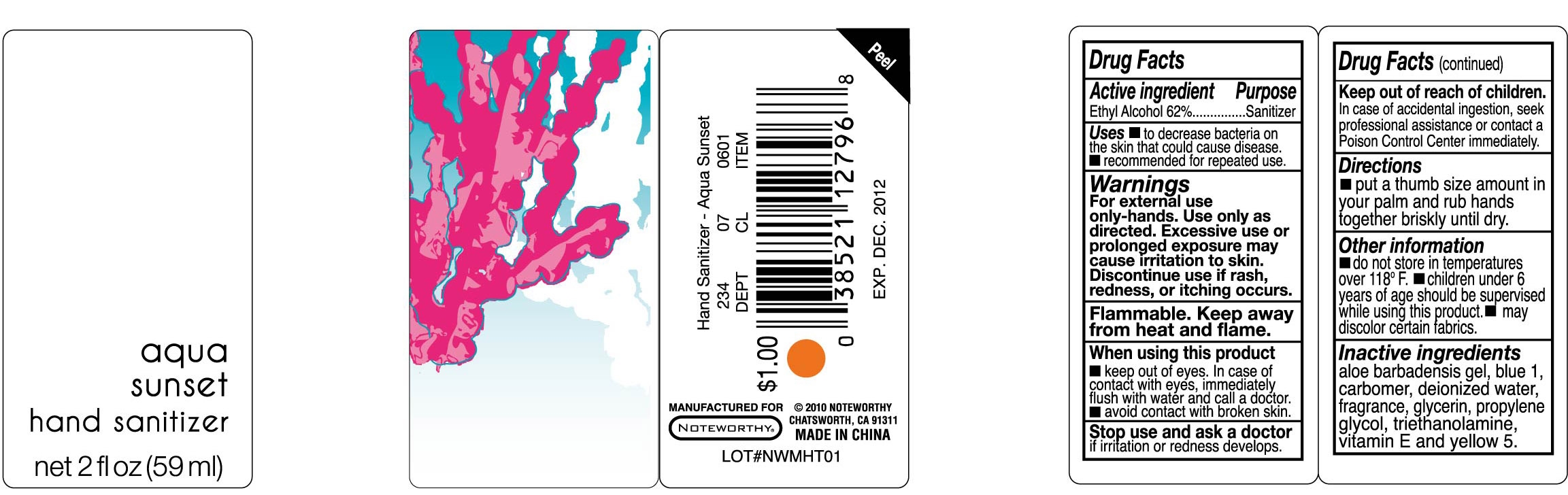 DRUG LABEL: Aqua Sunset Hand Sanitizer
NDC: 25225-023 | Form: LIQUID
Manufacturer: Unique Holding Group Inc
Category: otc | Type: HUMAN OTC DRUG LABEL
Date: 20101107

ACTIVE INGREDIENTS: ALCOHOL 62 g/100 g
INACTIVE INGREDIENTS: Water 35.5998 g/100 g; Propylene Glycol  0.5 g/100 g; Glycerin 1 g/100 g; ALOE VERA LEAF 0.01 g/100 g; CARBOMER HOMOPOLYMER TYPE C 0.33 g/100 g; ALPHA-TOCOPHEROL 0.01 g/100 g; TROLAMINE 0.35 g/100 g; FD&C BLUE NO. 1 0.0001 g/100 g; FD&C YELLOW NO. 5 0.0001 g/100 g

Drug Facts

Active Ingredient

Ethyl Alcohol 62%

Purpose:
Sanitizer

Uses:
To decrease the bacteria on the skin that could cause disease. Recommended for repeated use.

Warnings:
For external use only-hands.
Use only as directed.
Excessive use or prolonged exposure may cause irritation to the skin.
Discontinue use if irritation, redness, or itching occurs.
Flammable. Keep away from heat and flame

When Using This Product:

Keep out of eyes. In case of contact with eyes, flush immediately with water and call a doctor.

Avoid contact with broken skin

Stop Use And Ask A Doctor if irritation or redness develops

Keep Out of Reach of Children:
In case of accidental ingestion, seek professional assistance or contact a Poison Control Center immediately

Directions:

Put a thumb size amount in your palm and rub hands together briskly until dry

Other Information

Do not store in temperatures over 118F

Children under six years of age should be supervised while using this product.

May discolor certain fabrics

Inactive Ingredients
aloe barbadensis gel, carbomer, deionized water, Fragrance, glycerin, propylene glycol, D and C Blue No. 1, triethanolamine, and vitamin E, FD and C Yellow No. 5

PACKAGE LABEL

lab